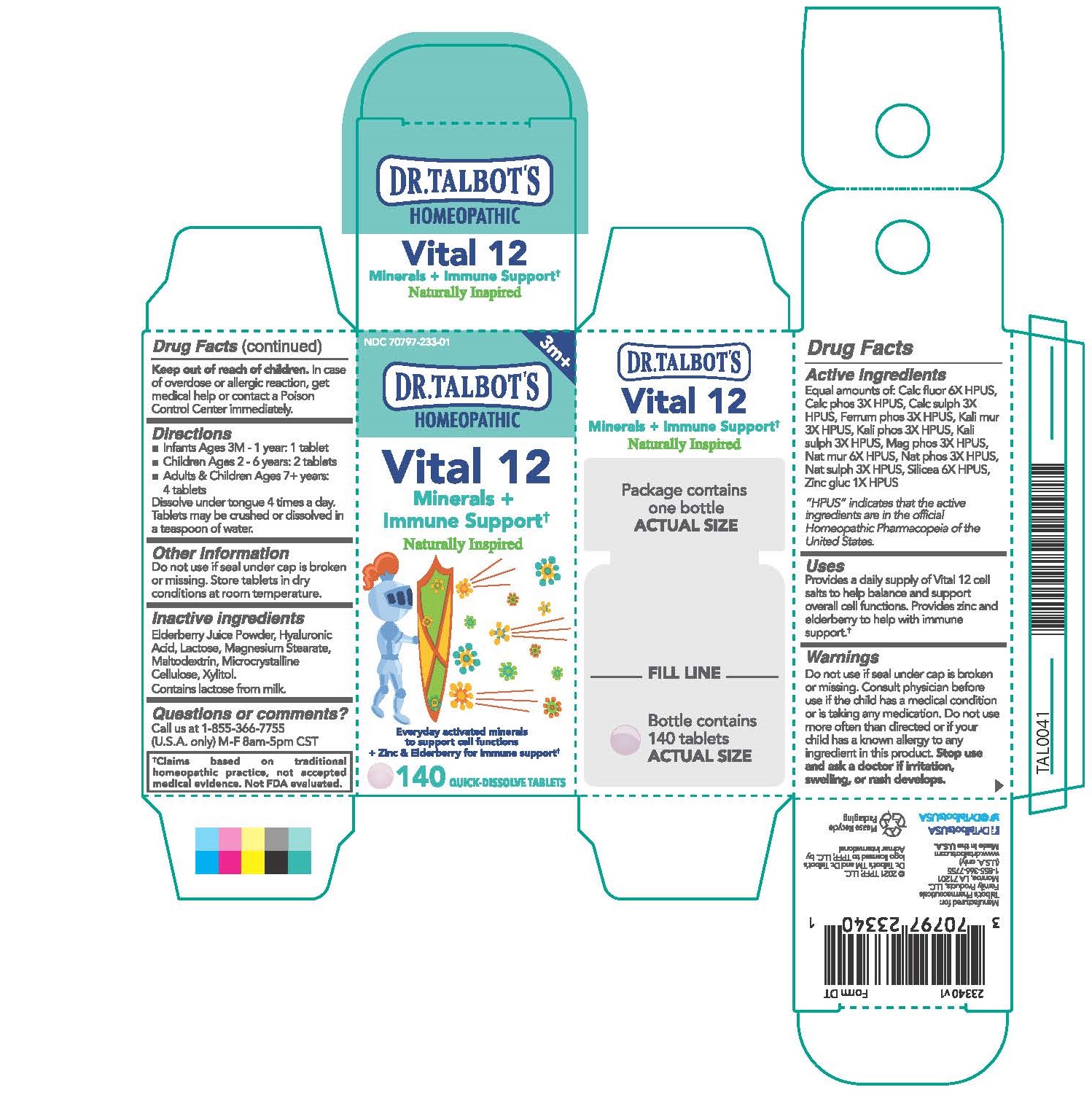 DRUG LABEL: Dr. Talbots Vital 12
NDC: 70797-233 | Form: TABLET, SOLUBLE
Manufacturer: Talbot's Pharmaceuticals Family Products, LLC
Category: homeopathic | Type: HUMAN OTC DRUG LABEL
Date: 20210428

ACTIVE INGREDIENTS: TRIBASIC CALCIUM PHOSPHATE 3 [hp_X]/1 1; SODIUM CHLORIDE 6 [hp_X]/1 1; SODIUM PHOSPHATE, DIBASIC, HEPTAHYDRATE 3 [hp_X]/1 1; ZINC GLUCONATE 1 [hp_X]/1 1; CALCIUM FLUORIDE 6 [hp_X]/1 1; POTASSIUM CHLORIDE 3 [hp_X]/1 1; POTASSIUM PHOSPHATE, DIBASIC 3 [hp_X]/1 1; SILICON DIOXIDE 6 [hp_X]/1 1; CALCIUM SULFATE ANHYDROUS 3 [hp_X]/1 1; FERROSOFERRIC PHOSPHATE 3 [hp_X]/1 1; POTASSIUM SULFATE 3 [hp_X]/1 1; SODIUM SULFATE 3 [hp_X]/1 1; MAGNESIUM PHOSPHATE, DIBASIC TRIHYDRATE 3 [hp_X]/1 1
INACTIVE INGREDIENTS: XYLITOL; HYALURONIC ACID; MAGNESIUM STEARATE; LACTOSE MONOHYDRATE; MICROCRYSTALLINE CELLULOSE; EUROPEAN ELDERBERRY JUICE

Active ingredients

Equal amounts of: Calc fluor 6X HPUS, Calc phos 3X HPUS, Calc sulph 3X HPUS, Ferrum phos 3X HPUS, Kali mur 3X HPUS, Kali phos 3X HPUS, Kali sulph 3X HPUS, Mag phos 3X HPUS, Nat mur 6X HPUS, Nat phos 3X HPUS, Nat sulph 3X HPUS, Silicea 6X HPUS, Zinc gluc 1X HPUS

"HPUS" indicates that the active ingredients are in the official Homeopathic Pharmacopeia of the United States.

PURPOSE

Provides a daily supply of Vital 12 cell salts to help balance and support overall cell functions. Provides zinc and elderberry to help with immune support.+

Warnings

Do not use if seal under cap is broken or missing. Consult physician before use if the child has medical condition or is taking any medication. Do not use more often than directed or if your child has a known allergy to any ingredient in this product.

Stop use and ask a doctor if irritation, swelling, or rash develops.

Keep out of reach of children. In case of overdose or allergic reaction, get medical help or contact a Poison Control Center immediately.

Directions

- Infant Ages 3m - 1 year: 1 tablet
- Children Ages 2 - 6 years: 2 tablets
- Adults & Children Ages 7+ years: 4 tablets

Dissolve under tongue 4 times a day. Tablets may be crushed or dissolved in a teaspoon of water.

Other information

Do not use if seal under cap is broken or missing. Store tablets in dry conditions at room temperature.

Inactive ingredients

Elderberry Juice Powder, Hyaluronic Acid, Lactose, Magnesium Stearate, Maltodextrin, Microcrystalline, Cellulose, Xylitol. Contains lactose from milk.

Questions or comments?

Call us at 1-855-366-7755 (U.S.A. only) M-F 8AM-5PM CST

+Claims based on traditional homeopathic practices, not accepted medical evidence. Not FDA evaluated.

INDICATIONS AND USAGE

Provides a daily supply of Vital 12 cell salts to help balance and support overall cell functions. Provides zinc and elderberry to help with immune support.+